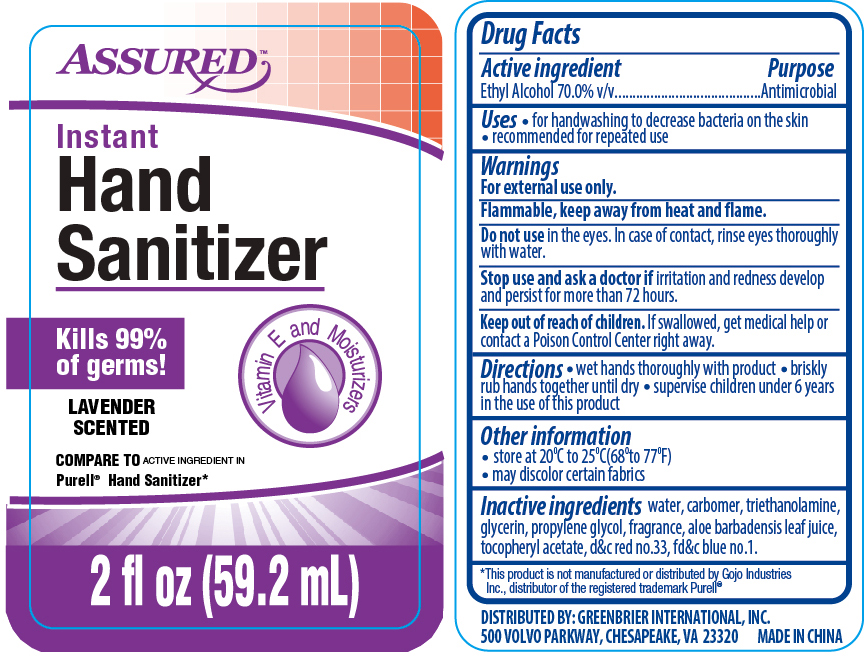 DRUG LABEL: Assured Instant
NDC: 58503-092 | Form: GEL
Manufacturer: China Ningbo Shangge Cosmetic Technology Corp.
Category: otc | Type: HUMAN OTC DRUG LABEL
Date: 20190918

ACTIVE INGREDIENTS: ALCOHOL 70 mL/100 mL
INACTIVE INGREDIENTS: WATER; CARBOMER COPOLYMER TYPE A; TROLAMINE; GLYCERIN; PROPYLENE GLYCOL; ALOE VERA LEAF; .ALPHA.-TOCOPHEROL ACETATE; D&C RED NO. 33; FD&C BLUE NO. 1

HAND SANITIZER BOX 2Z 3PK (Lavender)

Active Ingredient Purpose

Ethyl Alcohol 70.0% v/v ............... Antimicrobial

Uses

- for handwashing to decrease bacteria on the skin
- recommended for repeated use

Keep out of reach of children. If swallowed, get medical help or contact a Poison Control Center right away.

INDICATIONS AND USAGE

Instant Hand Sanitizer

Vitamin E and Moisturizers

Kills 99% of Germs!

Lavender Scented

Each: 2 fl oz (59.2 mL)

Directions

- wet hands thoroughly with product
- briskly rub hands together until dry
- supervise children under 6 years on the use of this product

Warnings

For external use only.

Flammable, keep away from heat and flame.

Do not use in the eyes. In case of contact, rinse eyes thoroughly with water.

Stop use and ask a doctor if irritation and redness develop and persist for more than 72 hours.

INACTIVE INGREDIENT

Inactive ingredients water, carbomer, triethanolamine, glycerin, propylene glycol, fragrance, aloe barbadensis leaf juice, tocopheryl acetate, d&c red no.33, fd&c blue no.1.